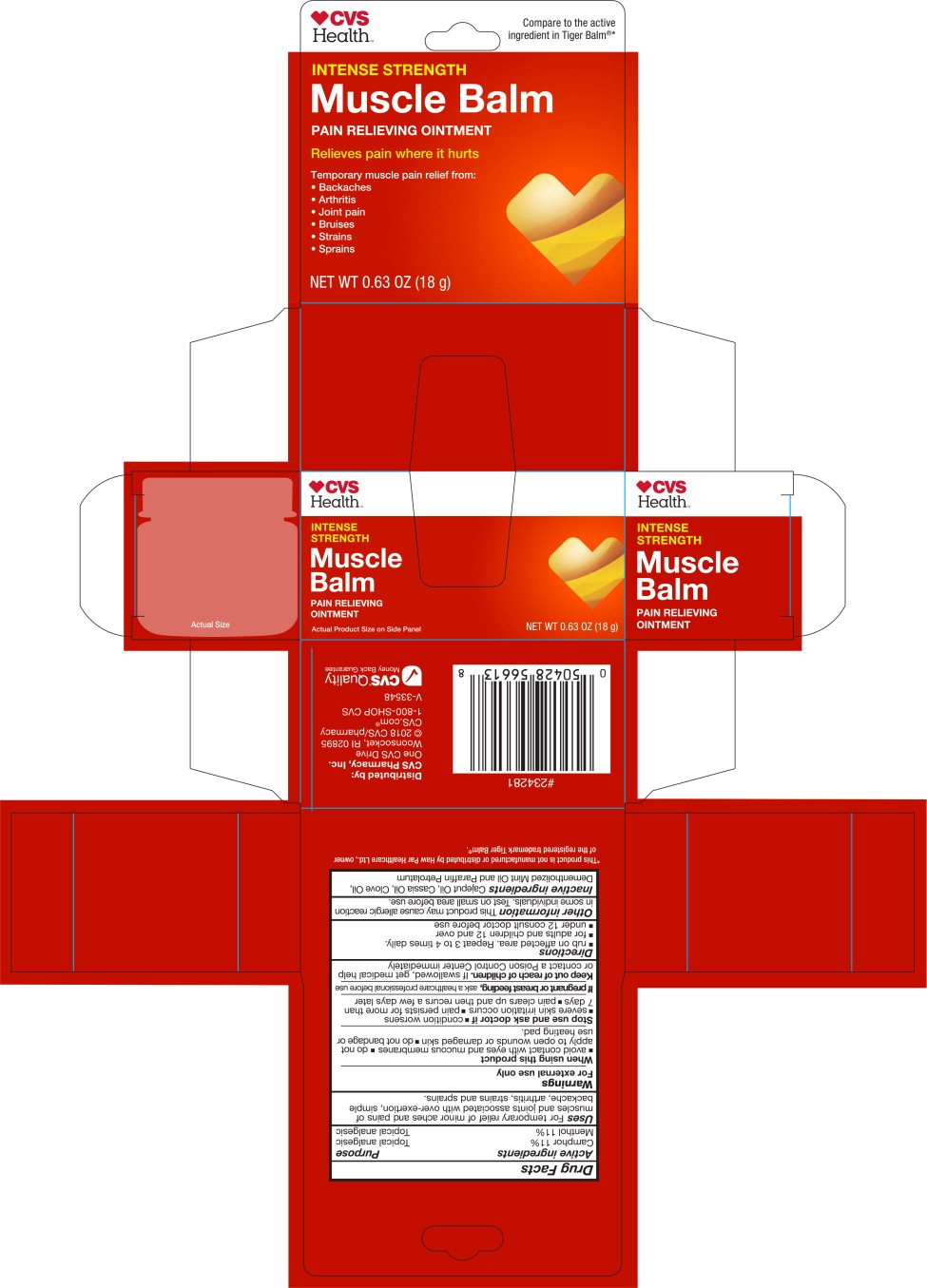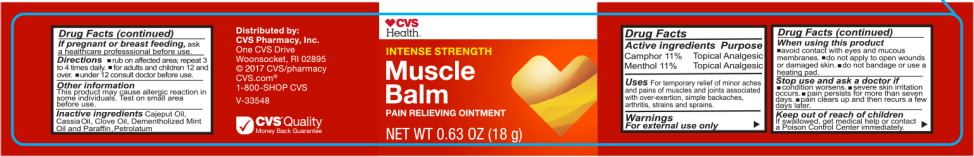 DRUG LABEL: CVS Health Muscle Balm
NDC: 66902-140 | Form: OINTMENT
Manufacturer: Natural Essentials, Inc.
Category: otc | Type: HUMAN OTC DRUG LABEL
Date: 20241004

ACTIVE INGREDIENTS: MENTHOL, UNSPECIFIED FORM 110 mg/1 g; CAMPHOR (SYNTHETIC) 110 mg/1 g
INACTIVE INGREDIENTS: CAJUPUT OIL; CHINESE CINNAMON OIL; CLOVE OIL; PEPPERMINT OIL TERPENELESS; PARAFFIN; PETROLATUM

Drug Facts

Active ingredients

Camphor 11 %

Menthol 11 %

Purpose

Topical analgesic

Topical analgesic

Uses

For temporary relief of minor aches and pains of muscles and joints associated with over-exertion, simple backache, arthritis, strains and sprains.

Warnings

For external use only

When using this product

- avoid contact with eyes and mucous membranes
- do not apply to open wounds or damaged skin
- do not bandage or use heating pad.

Stop use and ask doctor if

- condition worsens
- severe skin irritation occurs
- pain persists for more than 7 days
- pain clears up and then recurs a few days later

PREGNANCY OR BREAST FEEDING

If pregnant or breast feeding, ask a healthcare professional before use

Keep out of reach of children.If swallowed, get medical help or contact a Poison Control Center immediately

Directions

- rub on affected area. Repeat 3 to 4 times daily.
- for adults and children 12 and over
- under 12 consult doctor before use

Other information

This product may cause allergic reaction in some individuals. Test on small area before use.

Inactive ingredients

Cajeput Oil, Cassia Oil, Clove Oil, Dementholized Mint Oil and Paraffin Petrolatum

Principal Display Panel - 18 g Carton Label

CVS
Health™

Compare to the active
ingredient in Tiger Balm®*

INTENSE STRENGTH

Muscle Balm

PAIN RELIEVING OINTMENT

Relieves pain where it hurts

Temporary muscle pain relief from:

- Backaches
- Arthritis
- Joint pain
- Bruises
- Strains
- Sprains

NET WT 0.63 OZ (18 g)

Principal Display Panel - 18 g Jar Label

CVS
Health™

INTENSE STRENGTH

Muscle
Balm

PAIN RELIEVING OINTMENT

NET WT 0.63 OZ (18 g)